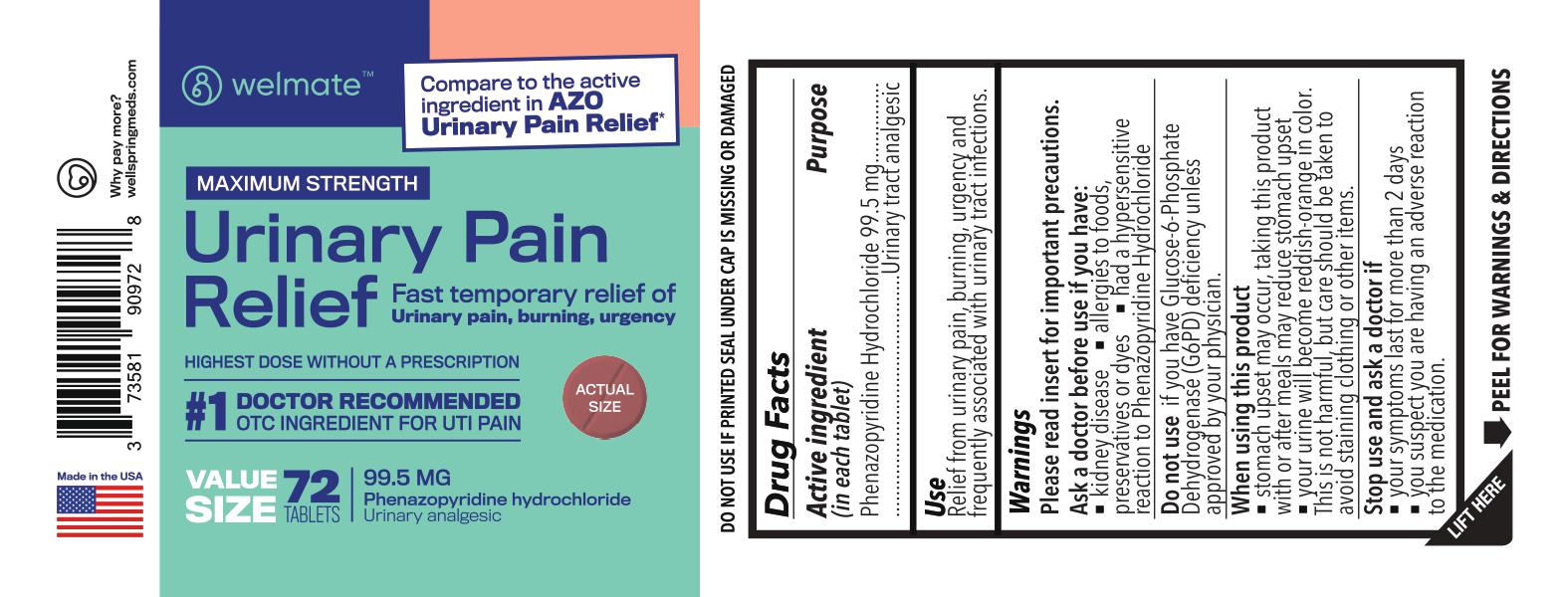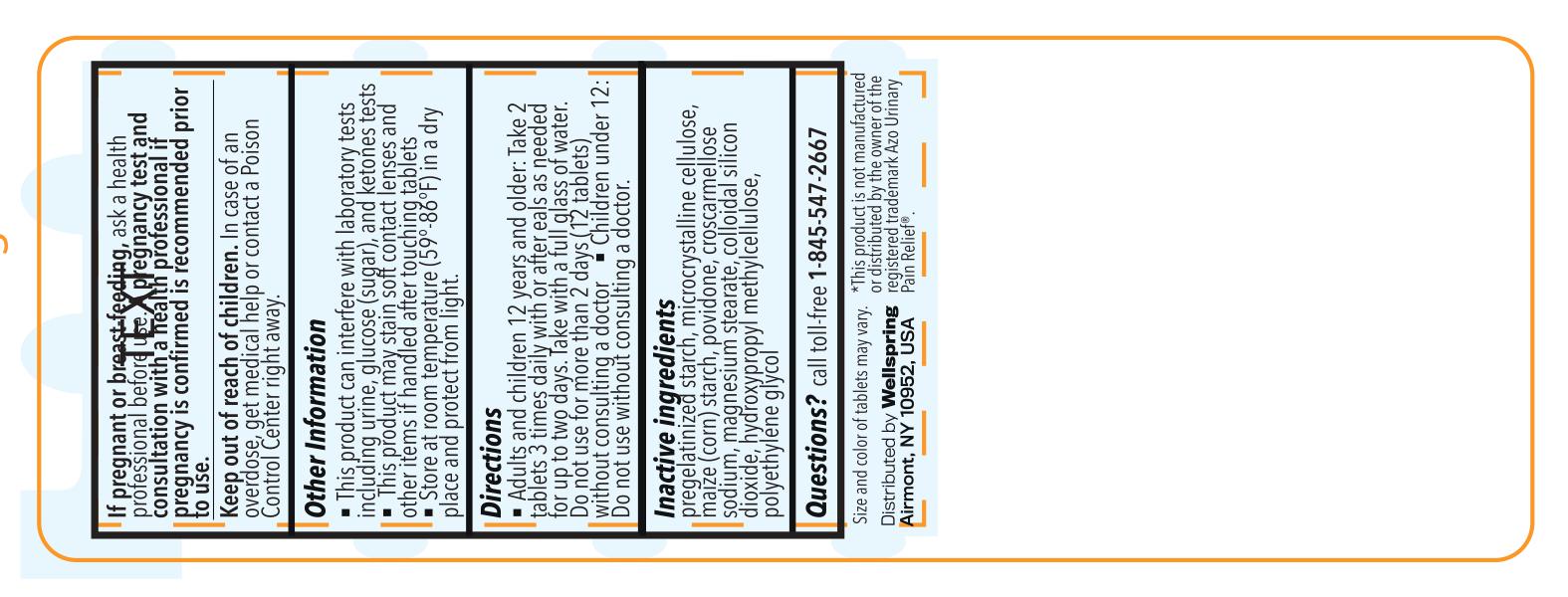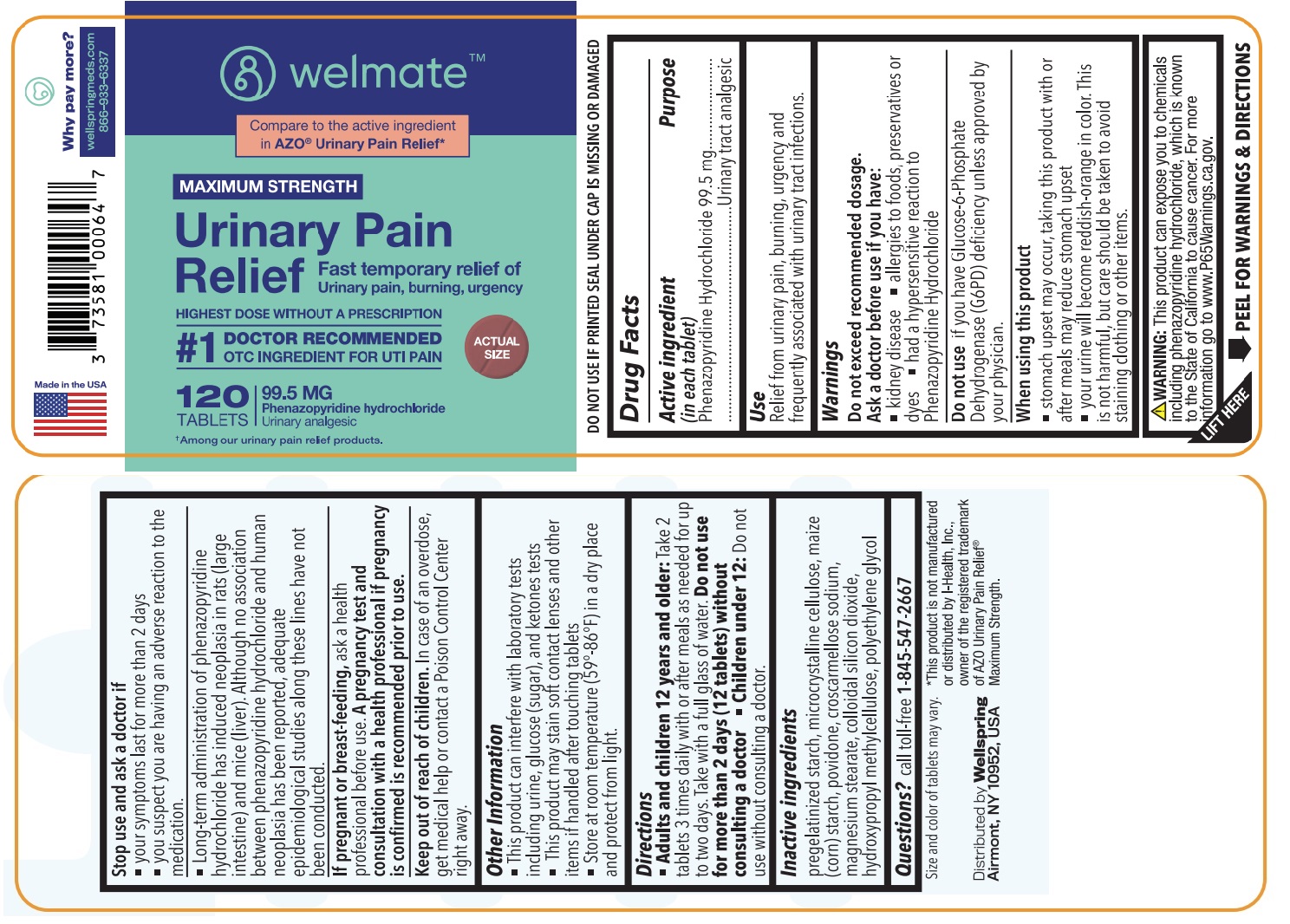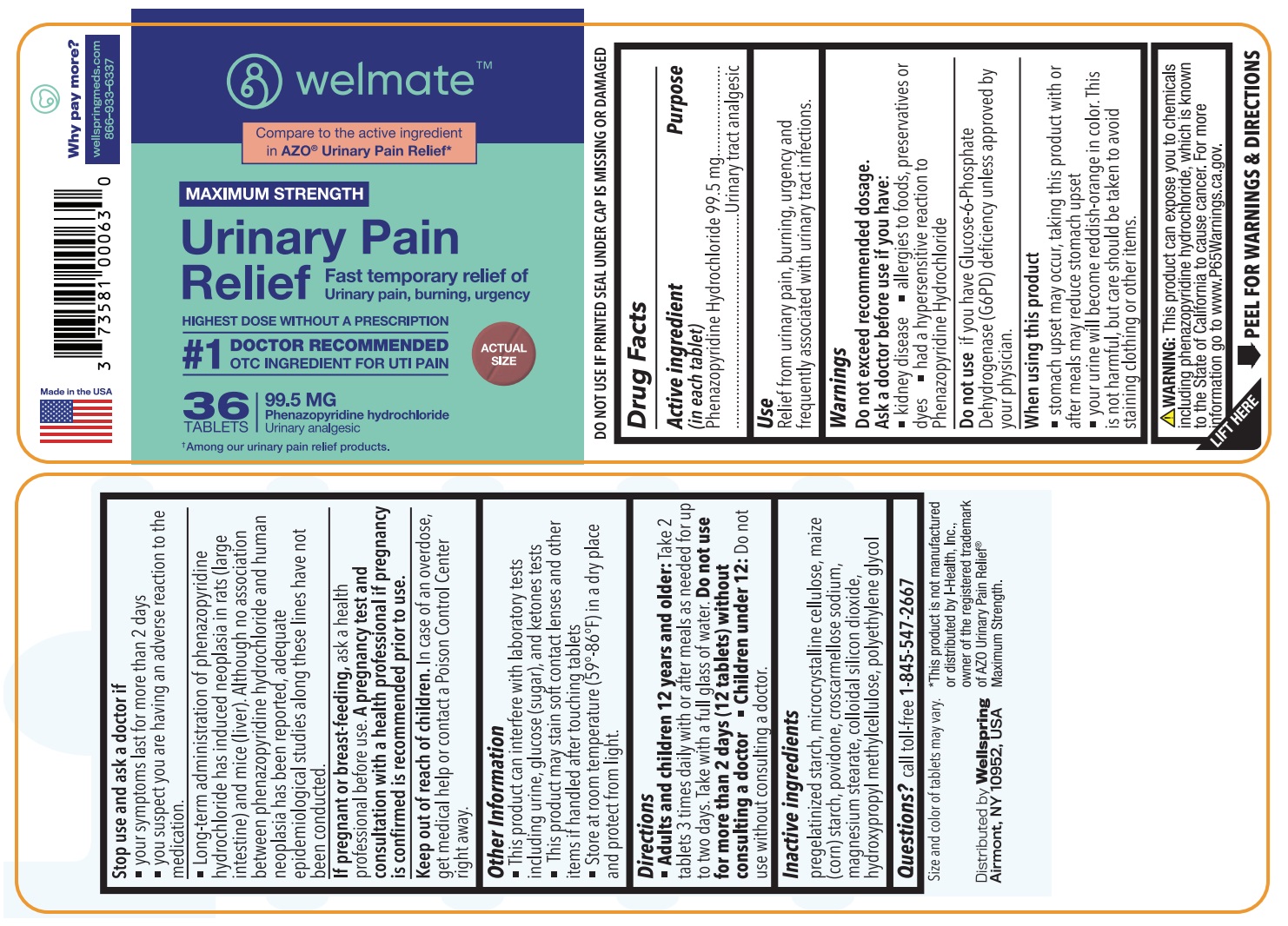 DRUG LABEL: Urinary Pain Relief
NDC: 73581-909 | Form: TABLET
Manufacturer: YYBA CORP
Category: otc | Type: HUMAN OTC DRUG LABEL
Date: 20250804

ACTIVE INGREDIENTS: PHENAZOPYRIDINE HYDROCHLORIDE 99.5 mg/1 1
INACTIVE INGREDIENTS: MAGNESIUM STEARATE; HYPROMELLOSE, UNSPECIFIED; STARCH, CORN; POLYETHYLENE GLYCOL 400; CELLULOSE, MICROCRYSTALLINE; POVIDONE K30; CROSCARMELLOSE SODIUM

YYBA (as PLD) - WELMATE - URINARY PAIN RELIEF (73581-909)

Active ingredient (in each tablet)

Phenazopyridine Hydrochloride 99.5 mg

Purpose

Urinary Tract Analgesic

Keep out of reach of children.In case of an overdose, get medical help or contact poison Control Center right away.

INDICATIONS AND USAGE

UseRelief from urinary pain, burning, urgency and frequency associated with urinary tract infections.

WARNINGS

Please read insert for important precautions.

Ask a doctor before use if you have:

■ kidney disease

■ allergies to foods, preservatives or dyes

■ had a hypersensitive reaction to Phenazopyridine Hydrochloride

Do not useif you have Glucose-6-Phosphate Dehydrogenase (G6PD) deficiency unless approved by your physician.

When using this product

■ stomach upset may occur, taking this product with or after meals may reduce stomach upset

■ your urine will become reddish-orange in color. This is not harmful, but care should be taken to avoid staining clothing or other items.

Stop use and ask a doctor if

■ your symptoms last for more than 2 days

■ you suspect you are having an adverse reaction to the medication

■ Long-term adminitration of phenazopyridine hydrochloride has induced neoplasia in rats (large instestine) andmice (liver). Although no association between phenazopyridine hydrochloride and human enoplasia has beeen reported, adequate epidemiological studies along these lines have not been conducted.

If pregnant or breast-feeding,ask a health professional before use. A pregnancy test and consultation with a health professional if pregnancy is confirmed is recommended prior to use.

Keep out of reach of children.In case of an overdose, get medical help or contact a Poison Control Center (1-800-222-1222) right away.

OTHER SAFETY INFORMATION

■ This product can interfere with laboratory tests including urine, glucose (sugar), and ketones tests

■ This product may stain contact lenses and other items if handled after touching tablets

■ long term administration of phenazopyridine HCI has induced neoplasia in rats (large intestine) and mice (liver). Although no association between phenazopyridine hydrochloride and human neoplasia has been reported, adequate epidemiological studies along these lines have not been conducted

■ Store at room temperature 15°-30°C (59°-86°F) in a dry place and protect from light

DOSAGE AND ADMINISTRATION

■Adults and children 12 years of age and over: Take 2 tablets 3 times daily with or after meals as needed for up to two days. Take with a full glass of water. Do not use for more than 2 days (12 tablets) without consulting a doctor

■ Children under 12: Do not use wihout consulting a doctor

INACTIVE INGREDIENT

pregelatinized starch, microcrystalline cellulose, maize (corn) starch, povidone, croscarmellose sodium, magnesium stearate, colloidal silicon dioxide, hydroxypropyl methylcellulose, polyethylene glycol

QUESTIONS

call toll-free 1-845-547-2667

Size and color of tablets may vary.

*This product is not manufactured or distributed by the owner of the registered trademark AZO Urinary Pain Relief®.

Distributed by: Wellspring

Airmont, NY 10952, USA